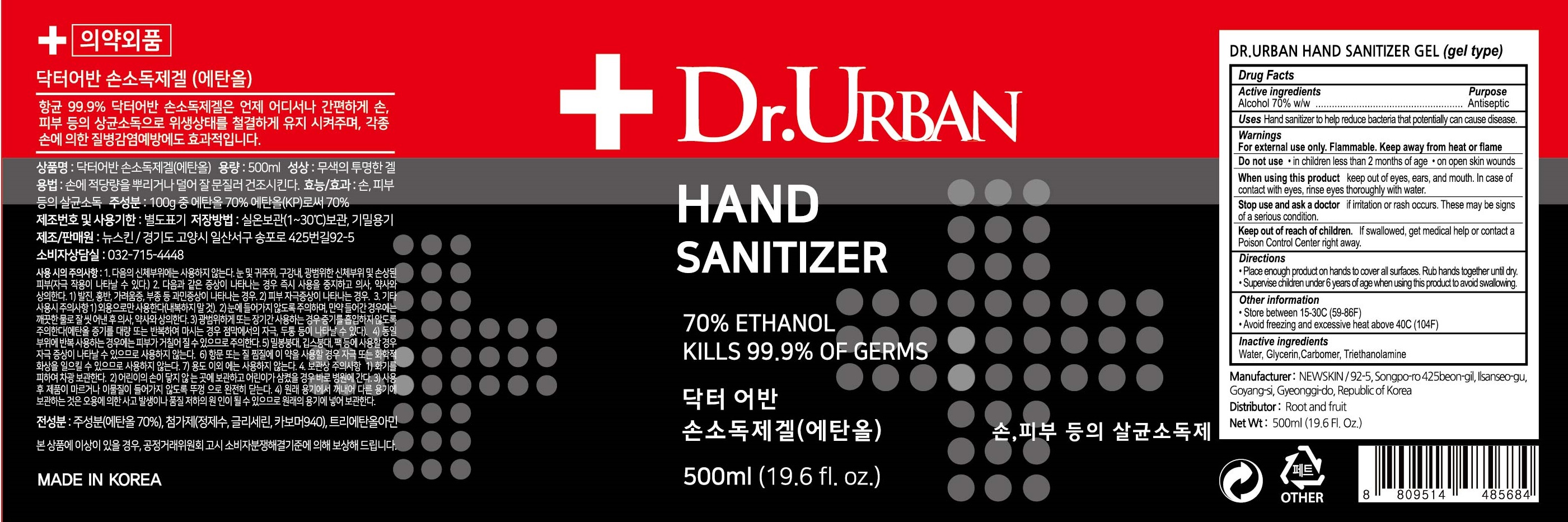 DRUG LABEL: Dr.URBAN Hand Sanitizer
NDC: 79282-010 | Form: GEL
Manufacturer: NEW SKIN
Category: otc | Type: HUMAN OTC DRUG LABEL
Date: 20200626

ACTIVE INGREDIENTS: Alcohol 350 g/500 mL
INACTIVE INGREDIENTS: Glycerin; CARBOMER HOMOPOLYMER, UNSPECIFIED TYPE; TROLAMINE

ACTIVE INGREDIENT

Alcohol 70% w/w

INACTIVE INGREDIENTS

Water, Glycerin, Carbomer, Triethanolamine

PURPOSE

Antiseptic

WARNINGS

For external use only. Flammable. Keep away from heat or flame
--------------------------------------------------------------------------------------------------------
Do not use
• in children less than 2 months of age
• on open skin wounds
--------------------------------------------------------------------------------------------------------
When using this product keep out of eyes, ears, and mouth. In case of contact with eyes, rinse eyes thoroughly with water.
--------------------------------------------------------------------------------------------------------
Stop use and ask a doctor if irritation or rash occurs. These may be signs of a serious condition.

KEEP OUT OF REACH OF CHILDREN

If swallowed, get medical help or contact a Poison Control Center right away.

Uses

Hand sanitizer to help reduce bacteria that potentially can cause disease.

Directions

• Place enough product on hands to cover all surfaces. Rub hands together until dry.

• Supervise children under 6 years of age when using this product to avoid swallowing.

Other information

• Store between 15-30C (59-86F)
• Avoid freezing and excessive heat above 40C (104F)